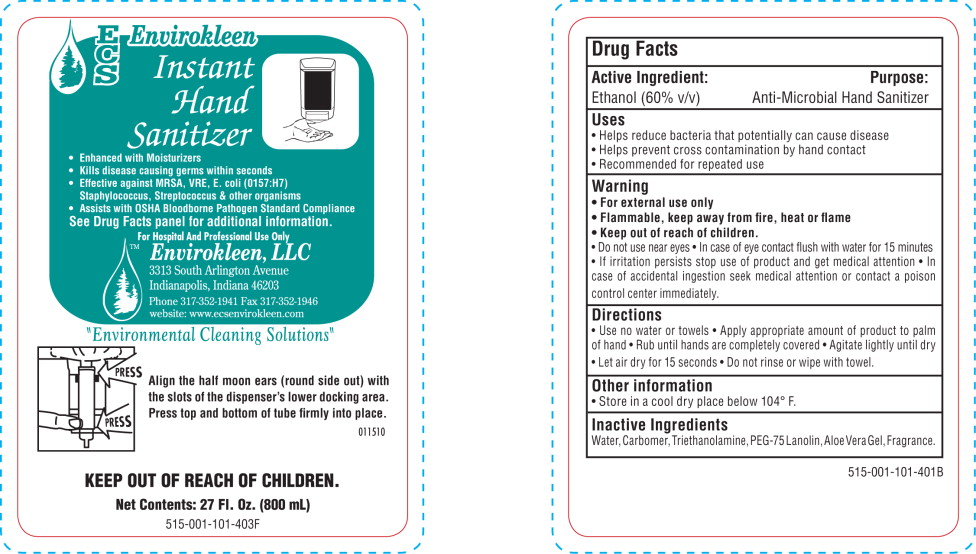 DRUG LABEL: Envirokleen Instant Hand Sanitizer
NDC: 50112-515 | Form: GEL
Manufacturer: EnviroKleen LLC
Category: otc | Type: HUMAN OTC DRUG LABEL
Date: 20110309

ACTIVE INGREDIENTS: alcohol 600 mL/1000 mL
INACTIVE INGREDIENTS: water; carbomer homopolymer type c; aloe; trolamine

ECS Envirokleen Instant Hand Sanitizer

Drug Facts

Active Ingredient:

Ethanol (60% v/v)

Purpose:

Anti-Microbial Hand Sanitizer

Uses

- Helps reduce bacteria that potentially can cause disease
- Helps prevent cross contamination by hand contact
- Recommended for repeated use

Warning

- For external use only
- Flammable, keep away from fire, heat, or flame

- Keep out of reach of children.
- Do not use near eyes
- In case of eye contact flush with water for 15 minutes
- If irritation persists stop use of product and get medical attention
- In case of accidental ingestion seek medical attention or contact a poison control center immediately.

Directions

- Use no water or towels
- Apply appropriate amount of product to palm of hand
- Rub until hands are completely covered
- Agitate lightly until dry
- Let air dry for 15 seconds
- Do not rinse or wipe with towel.

Other Information:

- Store in a cool dry place below 104° F.

Inactive Ingredients:

Water, Carbomer, Triethanolamine, PEG-75 Lanolin, Aloe Vera Gel, Fragrance.

Principal Display Panel

ECS Envirokleen Instant Hand Sanitizer

- Enhanced with Moisturizers
- Kills disease causing germs within seconds
- Effective against MRSA, VRE, E. coli (0157:H7)
  Staphylococcus, Streptococcus & other organisms
- Assists with OSHA Bloodborne Pathogen Standard Compliance

See Drug Facts panel for additional information.
For Hospital And Professional Use Only
Envirokleen, LLC
3313 South Arlington Avenue
Indianapolis, Indiana 46203
Phone 317-352-1941 Fax 317-352-1946
Website: www.ecsenvirokleen.com

“Environmental Cleaning Solutions”

Align the half moon ears (round side out) with
the slots of the dispenser's lower docking area.
Press top and bottom of tube firmly into place.

KEEP OUT OF REACH OF CHILDREN.